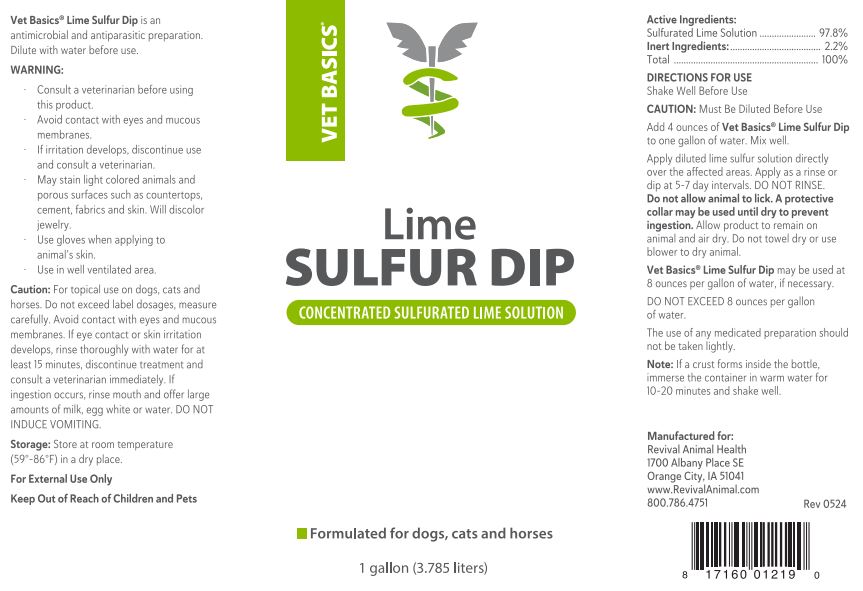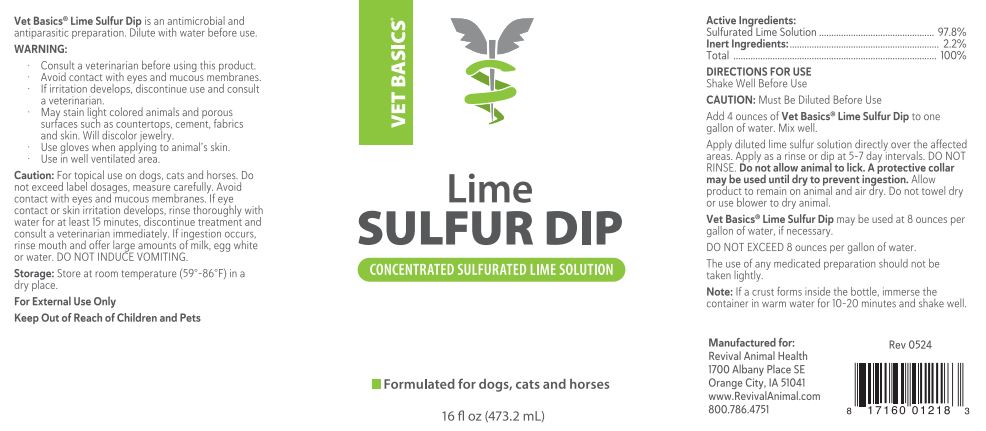 DRUG LABEL: Vet Basics Lime Sulfur
NDC: 86201-0001 | Form: SOLUTION, CONCENTRATE
Manufacturer: Revival Animal Health
Category: animal | Type: OTC ANIMAL DRUG LABEL
Date: 20240514

ACTIVE INGREDIENTS: CALCIUM POLYSULFIDE 290 mg/1 g
INACTIVE INGREDIENTS: water

INDICATIONS AND USAGE

Vet Basics® Lime Sulfur Dip is an antimicrobial and antiparasitic concentrated solution. Dilute with water before use.

WARNING:
• Consult a veterinarian before using this product.
• Avoid contact with eyes and mucous membranes.
• If irritation develops, discontinue use and consult a veterinarian.
• May stain light-colored animals and porous surfaces such as countertops, cement, fabrics and skin. Will discolor jewelry.
• Use gloves when applying to animal's skin.
• Use in a well-ventilated area.
Caution: For topical use only on dogs, cats and horses. Do not exceed label dosages, measure carefully. Avoid contact with eyes and mucous membranes.

If eye contact or skin irritation develops, rinse thoroughly with water for 15 minutes, discontinue treatment and consult a veterinarian immediately. If ingestion occurs, rinse mouth and offer large amounts of milk, egg white, or water. DO NOT INDUCE VOMITING.

For External Use Only

CAUTION: Must Be Diluted Before Use

STORAGE AND HANDLING

Storage: Store at room temperature (59°-86°F) in a dry place.

Keep Out of Reach of Children and Pets

Active Ingredients:
Sulferated Lime Solution ………….. 97.8%

INACTIVE INGREDIENT

Inert Ingredients …………………….. 2.2%
Total ………………………………… 100%

DIRECTIONS FOR USE
Shake Well Before Use
CAUTION: Must Be Diluted Before Use
Add 4 ounces of Vet Basics® Lime Sulfur Dip to one gallon of water. Mix well.
Apply diluted lime sulfur solution directly over the affected areas. Apply as a rinse or dip at 5-7 day intervals. DO NO RINSE. Do not allow animal to lick. A protective collar may be used until dry to prevent ingestion. Allow product to remain on animal and air dry. Do not towel dry or use blower to dry animal.
Vet Basics® Lime Sulfur Dip may be used at 8 ounces per gallon of water, if necessary.

Note: If a crust forms inside the bottle, immerse the container in warm water for 10-20 minutes and shake well.

WARNINGS AND PRECAUTIONS

DO NOT EXCEED 8 ounces per gallon of water.
The use of any medicated preparations should not be taken lightly.

Manufactured for:
Revival Animal Health
1700 Albany Place SE
Orange City, IA 51041
800.786.4751
Rev 0524
UPC 817160012183 16 oz

UPC 817160012190 1 gal

PACKAGE LABEL

Vet Basics® Lime Sulfur Dip

Concentrated Sulfurated Lime Solution

Formulated for dogs, cats and horses

16 fl oz (473.2 mL)

1 gallon (3.785 liters)